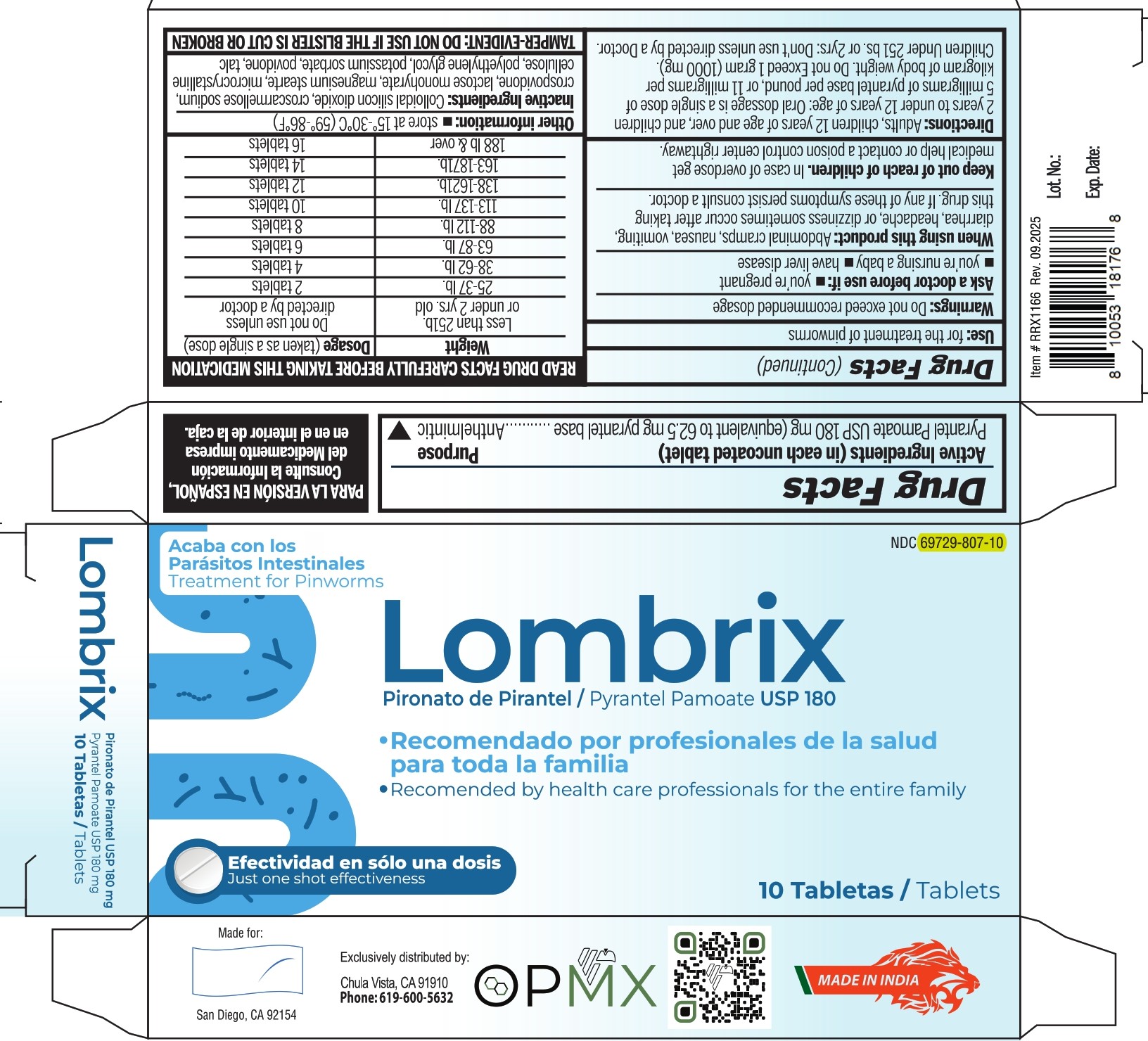 DRUG LABEL: Lombrix
NDC: 69729-807 | Form: TABLET
Manufacturer: OPMX LLC
Category: otc | Type: HUMAN OTC DRUG LABEL
Date: 20250924

ACTIVE INGREDIENTS: PYRANTEL PAMOATE 180 mg/1 1
INACTIVE INGREDIENTS: LACTOSE MONOHYDRATE; MICROCRYSTALLINE CELLULOSE; CROSPOVIDONE; CROSCARMELLOSE SODIUM; POVIDONE, UNSPECIFIED; POTASSIUM SORBATE; SILICON DIOXIDE; MAGNESIUM STEARATE; TALC; POLYETHYLENE GLYCOL 6000

Lombrix

Drug Facts

Active ingredient (in each uncoated tablet)

Pyrantel Pamoate USP 180 mg (equivalent to 62.5mg of pyrantel base)

Purpose

Antihelmintic

INDICATIONS AND USAGE

Use:for the treatment of pinworms

Warnings:Do not exceed recommended dosage

Ask a doctor before use if:

- you're pregnant
- you're nursing a baby
- you have liver disease

When using this product:abdominal cramps, nausea, vomiting, diarrhea, headache, or dizziness sometimes occur after taking this drug. If any of these symptoms persist consult a doctor.

Keep out of reach of children.In case of overdose, get medical help or contact a poison control center rightaway.

Directions:

Adults, children 12 years of age and over, and children 2 years to under 12 years: Oral dossage is a single dose of 5 mg of pyrantel base per pound or 11 mg of pyrantel base per kilogram of body weight. Do not Exceed 1 gram (1000mg). Children Under 25lbs. or 2yrs: Don't use unless directed by a doctor.

READ PACKAGE INSERT CAREFULLY BEFORE TAKING THIS MEDICATION

Weight | Dosage(taken as a single dose)
Less than 25 lb. or under 2 yrs. old | Do not use unless directed by a doctor
25-37 lb. | 2 tablets
38-62 lb. | 4 tablets
63-87 lb. | 6 tablets
88-112 lb. | 8 tablets
113-137 lb. | 10 tablets
138-162 lb. | 12 tablets
163-187 lb. | 14 tablets
188 lb & over | 16 tablets

Other information:

- store at 15°-30°C (59°-86°F)

INACTIVE INGREDIENT

Inactive ingredients:Colloidal silicon dioxide, croscarmellose sodium, crospovidone, lactose monohydrate, magnesium stearate, microcrystalline cellulose, polyethylene glycol, potassium sorbate, povidone, talc.

OTHER SAFETY INFORMATION

TAMPER-EVIDENT: DO NOT USE IF THE BLISTER IS CUT OR BROKEN

Exclusively distributed by

OPMX

Chula Vista, CA 91910

Questions or comments:

619-600-5632

MADE IN INDIA

PACKAGE LABEL

NDC 69729-807-10

Lombrix

Pyrantel Pamoate Tablets 180 mg

TREATMENT FOR PINWORMS

- Recommended By Health Care Professionals ForThe Entire Family

10 Tablets